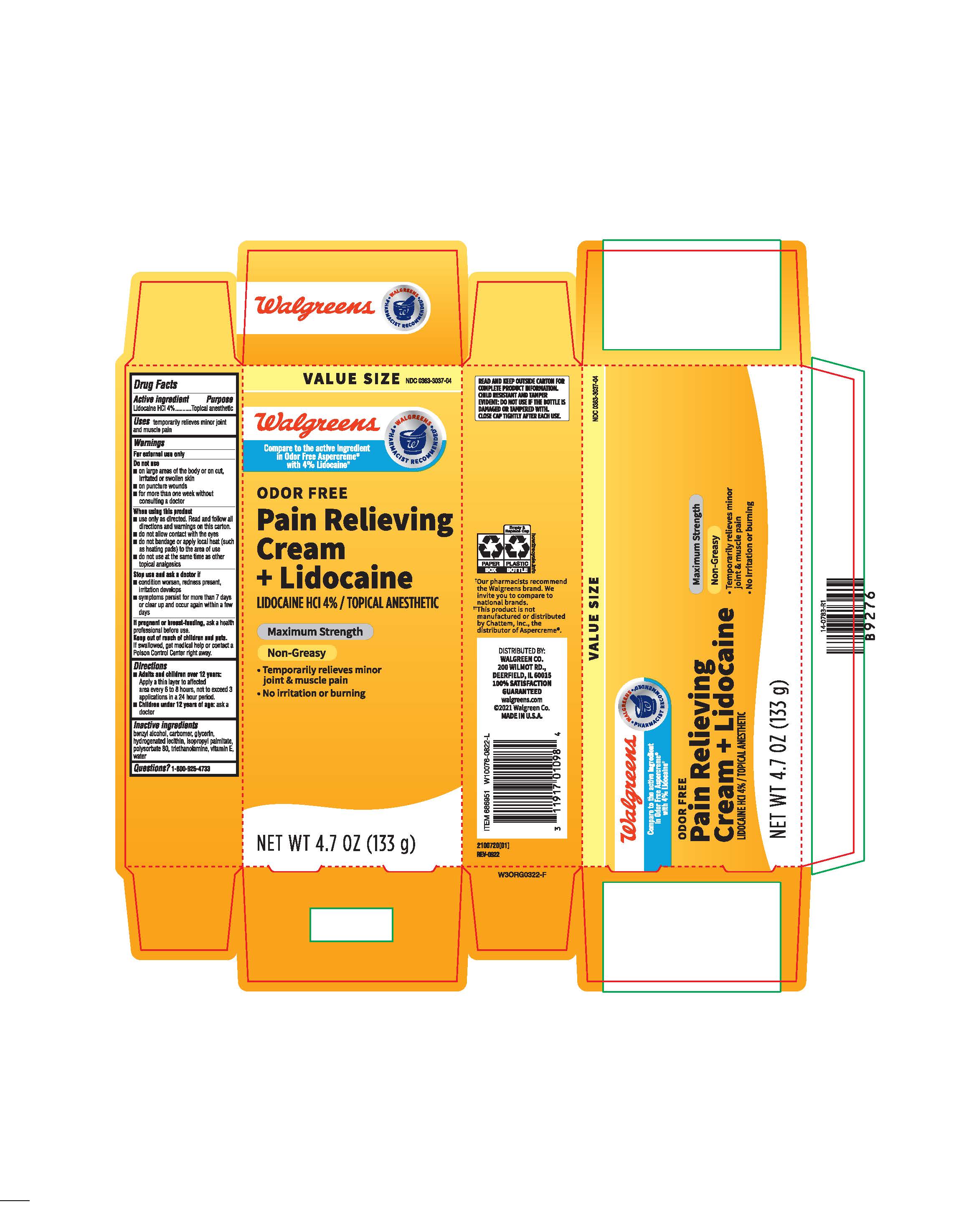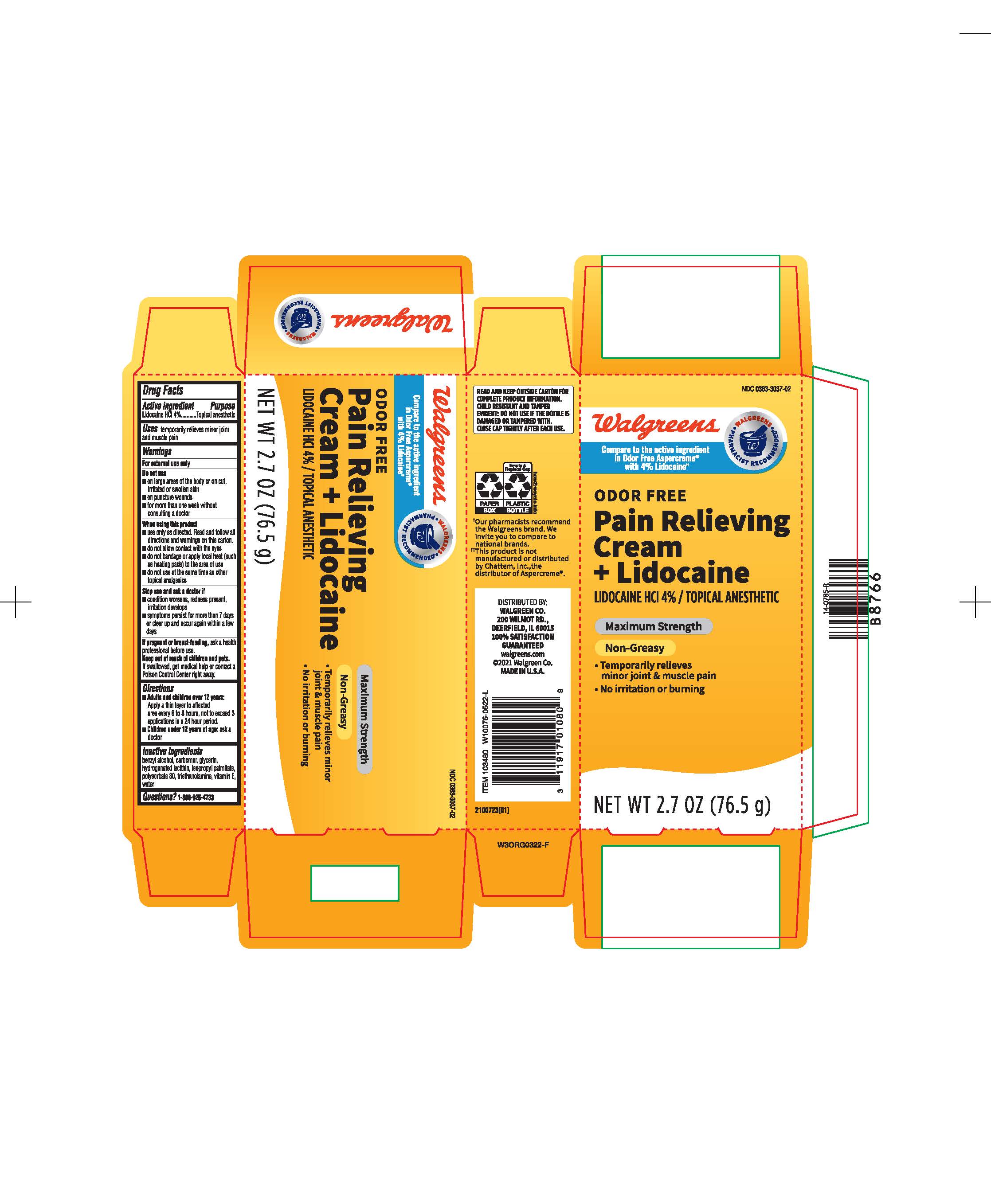 DRUG LABEL: Walgreens Pain Relieving Cream
NDC: 0363-3037 | Form: CREAM
Manufacturer: Walgreens
Category: otc | Type: HUMAN OTC DRUG LABEL
Date: 20231031

ACTIVE INGREDIENTS: LIDOCAINE HYDROCHLORIDE 4 g/100 g
INACTIVE INGREDIENTS: POLYSORBATE 80; GLYCERIN; CARBOMER 940; TROLAMINE; TOCOPHEROL; WATER; ISOPROPYL PALMITATE; HYDROGENATED SOYBEAN LECITHIN; BENZYL ALCOHOL

Walgreens Pain Relieving Cream + Lidocaine

ACTIVE INGREDIENT

Lidocaine HCl 4%

PURPOSE

Topical Anesthetic

INDICATIONS AND USAGE

temporarily relieves minor joint and muscle pain

WARNINGS

For external use only

DO NOT USE

- On large areas of the body or on cut,irritated or swollen skin
- On punctured wounds
- for more than one week without consulting a doctor

WHEN USING

- Use only as directed. Read and follow all directions and warnings on this carton
- do not allow contact with eyes
- do not bandage or apply local heat to the area of use
- do not use at the same time as other topical analgesics

STOP USE

- the condition worsens, redness present, irritation develops
- symptoms persist for more than 7 days or clear up and occur again within a few days

PREGNANCY OR BREAST FEEDING

ask a health professional before use

Keep out of reach of children and pets

If swallowed, get medical help or contact a Poison Control Center right way

DOSAGE AND ADMINISTRATION

Adults and children over 12 years: Apply a thin layer to the affected area every 6 to 8 hours, not exceeding 3 applications in a 24 hour period.

Children under 12 years of age: ask a doctor

INACTIVE INGREDIENT

benzyl alcohol, carbomer, glycerin, hydrogenated lecithin, isopropyl palmitate, polysorbate 80, triethanolamine, vitamin E, water

QUESTIONS

1800-925-4733